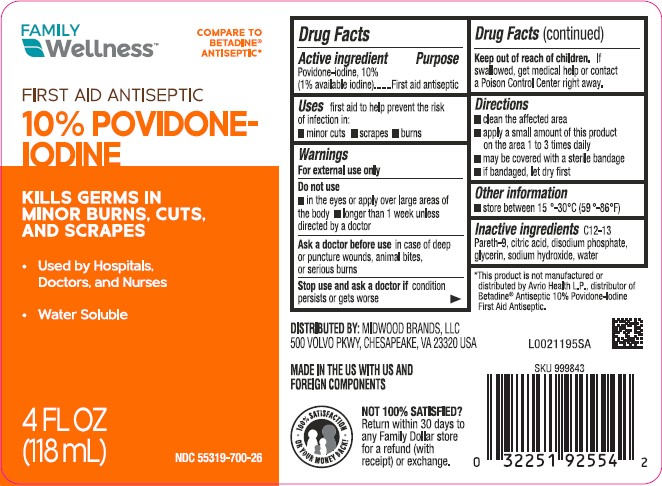 DRUG LABEL: First Aid Antiseptic
NDC: 55319-700 | Form: SOLUTION
Manufacturer: Family Dollar Stores, Inc
Category: otc | Type: HUMAN OTC DRUG LABEL
Date: 20260224

ACTIVE INGREDIENTS: POVIDONE-IODINE 10 mg/1 mL
INACTIVE INGREDIENTS: C12-13 PARETH-9; CITRIC ACID MONOHYDRATE; SODIUM PHOSPHATE, DIBASIC, ANHYDROUS; GLYCERIN; SODIUM HYDROXIDE; WATER

Family Wellness 050.002/050AE
Povidone-Iodine Solution, 10%

Active ingredient

Povidone-iodine, 10% (1% available iodine)

Purpose

First aid antiseptic

Uses

first aid to help prevent the risk of infection in:

- minor cuts
- scrapes
- burns

Warnings

For external use only

Do not use

- in the eyes or aply over large areas of the body
- longer than 1 week unless directed by a doctor

Ask a doctor before use

in case of deep or puncture wounds, animal bites, or serious burns

Stop use and ask a doctor if

condition persists or gets worse

Keep out of reach of children

If swallowed, get medical help or contact a Poison Control Center right away.

Directions

- clean the affected area
- apply a small amount of this product on the area 1 to 3 times daily
- may be covered with a sterile bandage
- if bandaged, let dry first

Other information

- store between 15°-30° C (59°-86F)

inactive ingredients

C12-13 Pareth-9, citric acid, disodium phosphate, glycerin, sodium hydroxide, water

Adverse Event

DISTRIBUTED BY: MIDWOOD BRANDS, LLC

500 VOLVO PARKWAY

CHESAPEAKE, VA 23320

100% SATISFICATION OR YOUR MONEY BACK!*

NOT 100% SATISFIED?

Return within 30 day to any Family Dollar store for a refund (with receipt) or exchange.

Disclaimer

*This product is not manufactured or distributed by Avrio Health L.P., distributor of Betadine®Antiseptic 10% Povidone-Iodine First Aid Antiseptic.

MADE IN THE US WITH US AND FOREIGN COMPONENTS

Principal display panel

FAMILY WELLNESS™

COMPARE TO BETADINE® ANTISEPTIC*

FIRST AID ANTISEPTIC

10% POVIDONE-IODINE

KILLS GERMS IN MINOR BURNS, CUTS, AND SCRAPES

- Used by hospitals, Doctors, and Nurses
- Water Soluble

NDC 55319-700-26

4 FL OZ (118 mL)